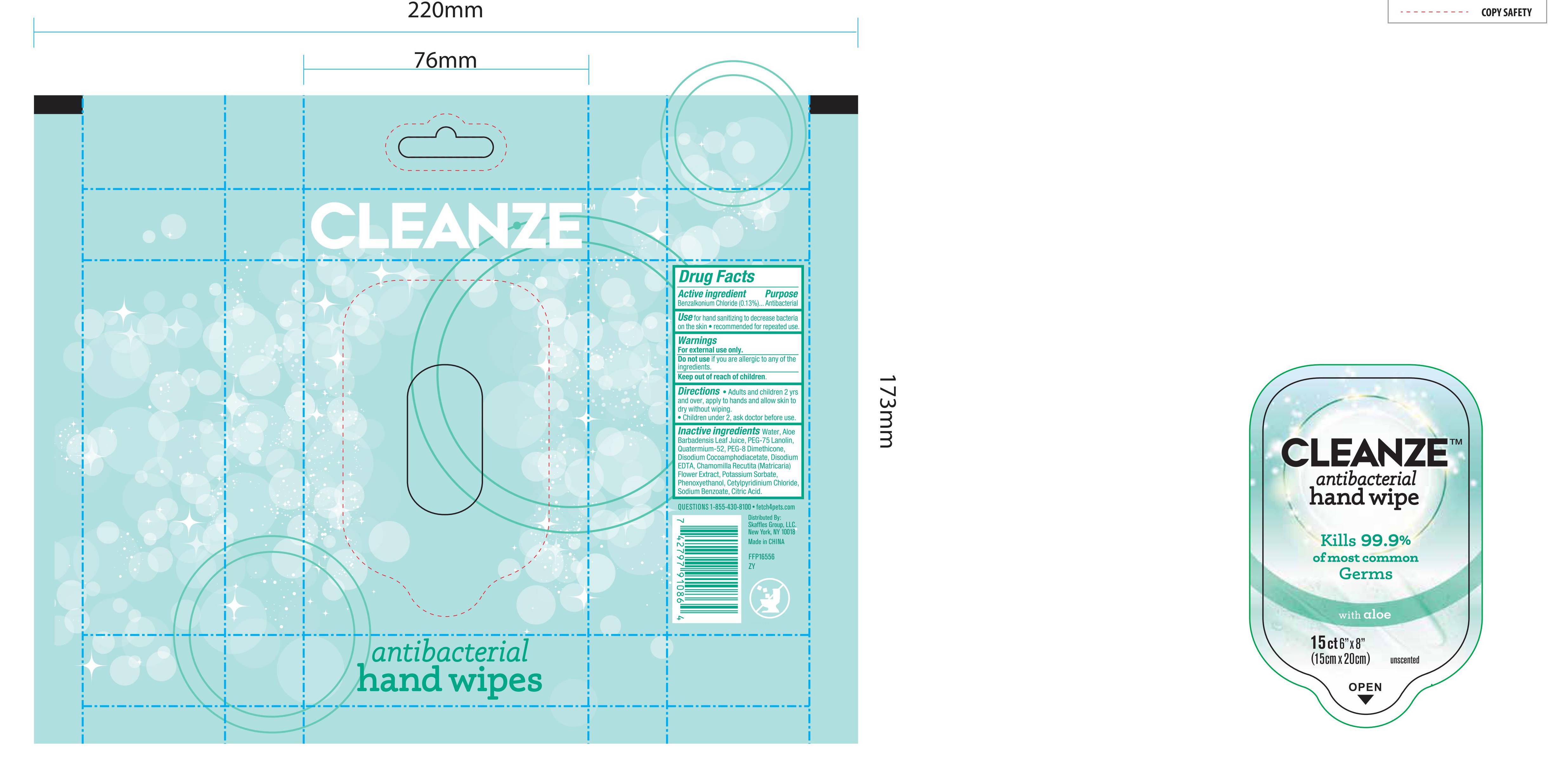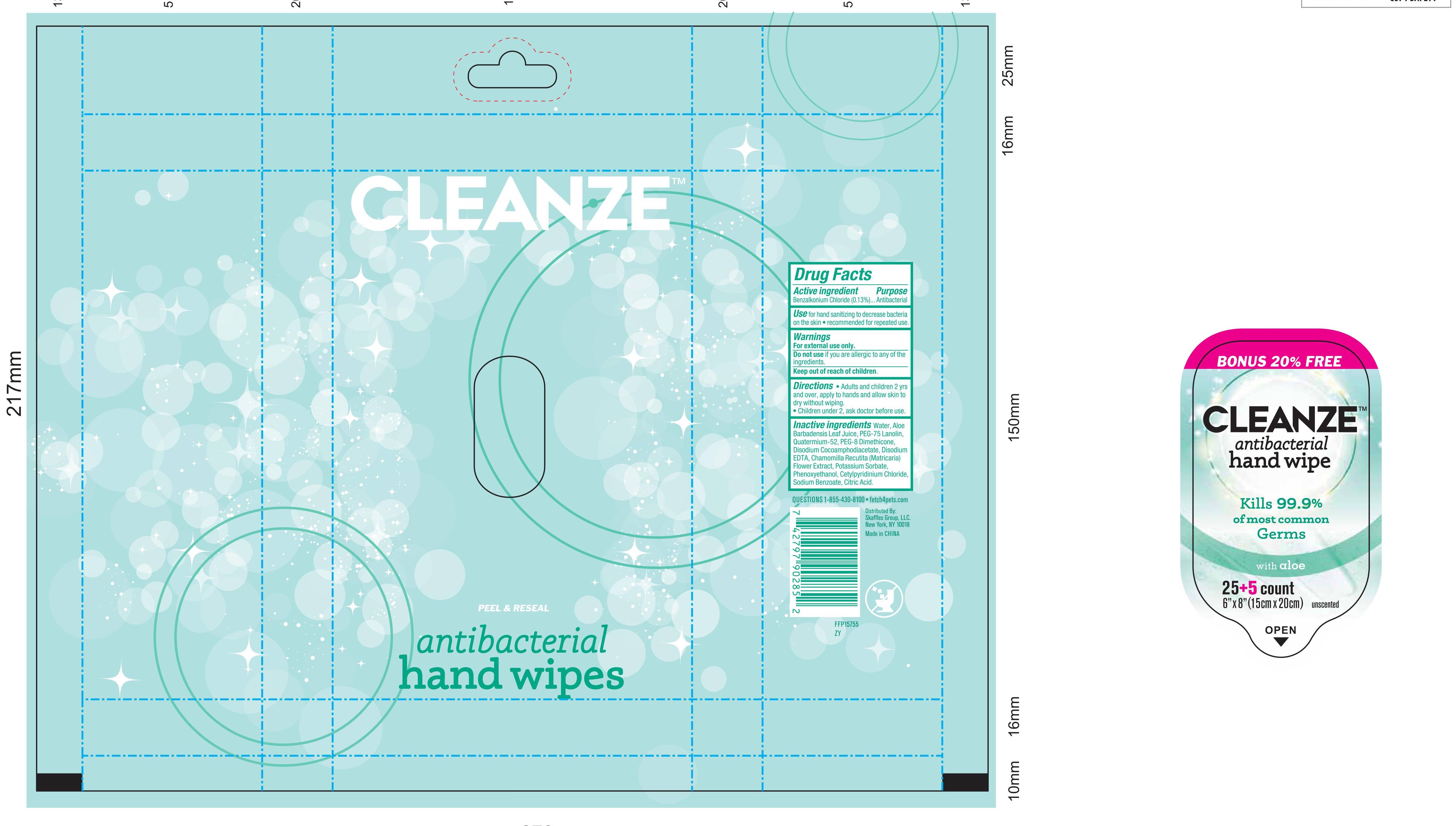 DRUG LABEL: HAND SANITIZING WIPES
NDC: 77720-011 | Form: CLOTH
Manufacturer: Skaffles Group Limited Liability Company
Category: otc | Type: HUMAN OTC DRUG LABEL
Date: 20200923

ACTIVE INGREDIENTS: BENZALKONIUM CHLORIDE 0.13 g/100 g
INACTIVE INGREDIENTS: WATER; QUATERNIUM-52; PEG-75 LANOLIN; ALOE VERA LEAF; CITRIC ACID MONOHYDRATE; CETYLPYRIDINIUM CHLORIDE; PEG-8 DIMETHICONE; DISODIUM COCOAMPHODIACETATE; DISODIUM EDTA-COPPER; CHAMOMILE; POTASSIUM SORBATE; PHENOXYETHANOL; SODIUM BENZOATE

77720-011 HAND SANITIZING WIPES 0.13% BENZALKONIUM CHLORIDE

Active Ingredient

Benzalkonium Chloride 0.13%

Purpose

Antibacterial

USE

For hand washing to decrease bacteria on the skin.
Recommended for repeated use.

Warning

For external use only. Do not use if you are allergic to
any of the ingredients.

Keep out of reach of children.

Directions

Directions● Adults and children 2 yrs and over,
apply to hands and allow skin to dry without wiping.
●Children under 2, ask doctor before use.

Inactive ingredients

Inactive ingredients Water, Aloe Barbadensis Leaf Juice,
PEG-75 Lanolin, Quatermium-52, PEG-8 Dimethicone, Disodium
Cocoamphodiacetate, Disodium EDTA, Chamomilla Recutita
(Matricaria) Flower Extract, Potassium Sorbate, Phenoxyethanol,
Cetylpyridinium Chloride, Sodium Benzoate, Citric Acid.